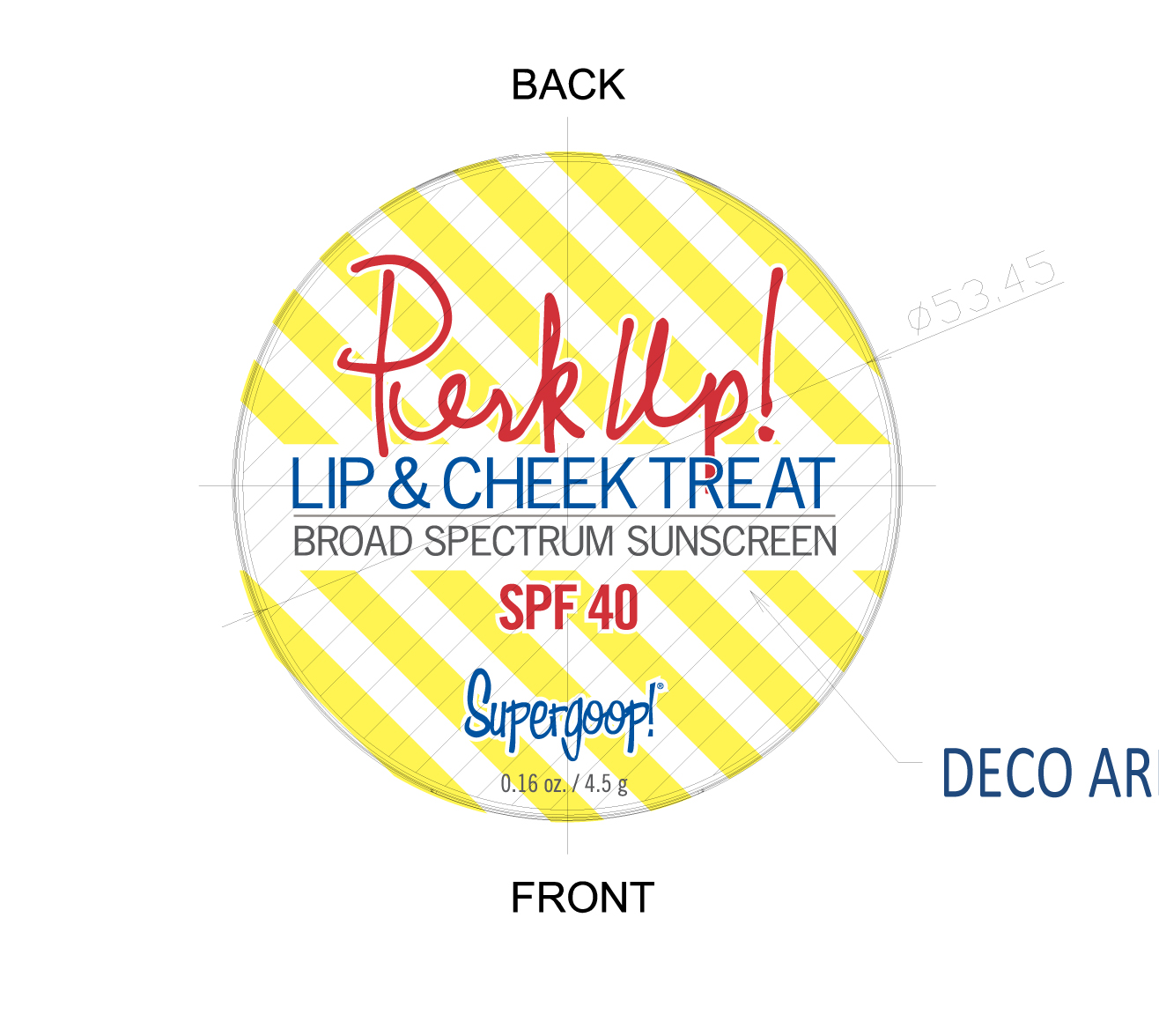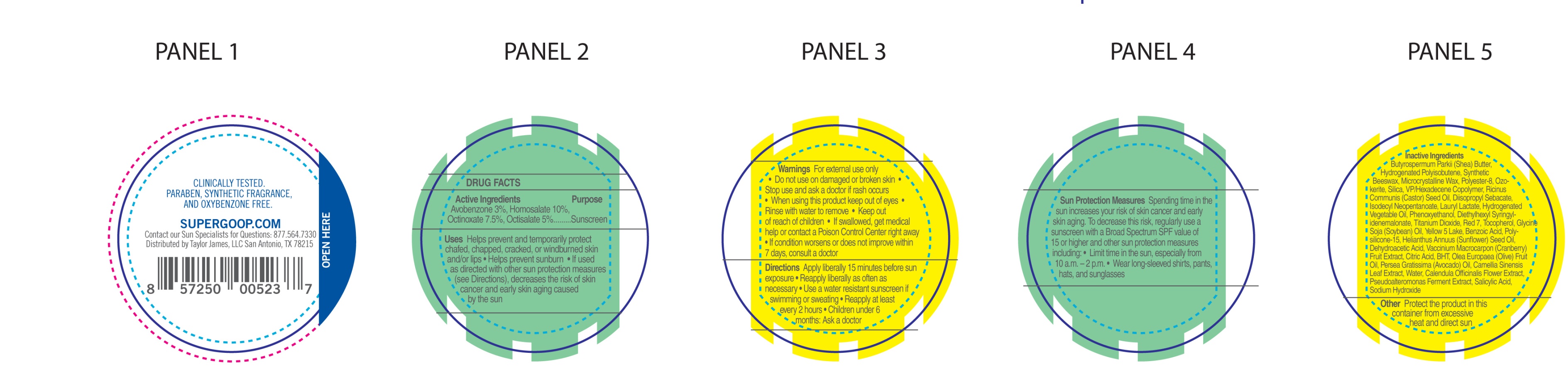 DRUG LABEL: Lip and Cheek Treat Broad Spectrum SPF 40
NDC: 75936-503 | Form: STICK
Manufacturer: TAYLOR JAMES, LTD.
Category: otc | Type: HUMAN OTC DRUG LABEL
Date: 20170105

ACTIVE INGREDIENTS: AVOBENZONE 3 g/100 g; HOMOSALATE 10 g/100 g; OCTINOXATE 7.5 g/100 g; OCTISALATE 5 g/100 g
INACTIVE INGREDIENTS: SHEA BUTTER; HYDROGENATED POLYBUTENE (1300 MW); SYNTHETIC WAX (1200 MW); MICROCRYSTALLINE WAX; POLYESTER-8 (1400 MW, CYANODIPHENYLPROPENOYL CAPPED); CERESIN; SILICON DIOXIDE; VINYLPYRROLIDONE/HEXADECENE COPOLYMER ; CASTOR OIL; DIISOPROPYL SEBACATE; ISODECYL NEOPENTANOATE; LAURYL LACTATE; PHENOXYETHANOL; DIETHYLHEXYL SYRINGYLIDENEMALONATE; TITANIUM DIOXIDE; D&C RED NO. 7; TOCOPHEROL; SOYBEAN OIL; BENZOIC ACID; POLYSILICONE-15; SUNFLOWER OIL; DEHYDROACETIC ACID; CRANBERRY; CITRIC ACID MONOHYDRATE; BUTYLATED HYDROXYTOLUENE; OLIVE OIL; AVOCADO OIL; GREEN TEA LEAF; WATER; CALENDULA OFFICINALIS FLOWER; SALICYLIC ACID; SODIUM HYDROXIDE

Lip & Cheek Treat Broad Spectrum Sunscreen SPF 40

Active Ingredients Purpose

Avobenzone 3%, Homosalate 10%,

Octinoxate 7.5%, Octisalate 5% ....... Sunscreen

Uses

Helps prevent and temporarily protect chafed, chapped, cracked, or windburned skin and/or lips

- Helps prevent subnurn
- If use as directed with other sun pretction measures (see Directions), decreases the risk of skin cancer and early skin aging caused by the sun

Keep out of reach of children

Stop use and ask a doctor if rash occurs

Warnings

For external use only

- Do not use on damaged or broken skin
- when using this product keep out of eyes
- Rinse with water to remove
- If swallowed, get medical help or contact a Posion Control Center right away
- If condition worsens or does not improve within 7 days, consult a doctor

Directions

Apply liberally 15 minutes before sun exposure

- Reapply liberally as oftenas necessary
- Use a water resistant sunscreen if swimming or sweating
- Reapply at least every 2 hours
- Children under 6 months: Ask a doctor

Sun Protection Measures Spending time in the sun increases your risk of skin cancer and early skin aging. To decrease this risk, regularly use a sunscreen with a Broad Spectrum SPF value of 15 or higher and other sun protection measures including:

- Limit time in the sun, especially from 10 a.m. - 2 p.m.
- Weare long-sleeved shirts, pants, hats, and sunglasses

INACTIVE INGREDIENT

Butyrospermum Parkii (Shea) Butter, Hydrogenated Polyisobutene, Synthetic Beeswax, Microcrystalline Wax, Polyester-8, Ozokerite, Silica, VP/Hexadecene Copolymer, Ricinus Communis (Castor) Seed Oil, Diisopropyl Sebacate, Isodecyl Neopentanoate, Lauryl Lactate, Hydorgenated Vegetable Oil, Phenoxyethanol, Diethylhexyl Syringylidenemalonate, Titanium Dioxide, Red 7, Tocopherol, Glycine Soja (Soybean) Oil, Yellow 5 Lake, Benzoic Acid, Polysilicone-15, Helianthus Annuus (Sunflower) Seed Oil, Dehydoacetic Acid, Vaccinium Macrocarpon (Cranberry) Fruit Extract, Citric Acid, BHT, Olea Europaea (Olive) Fruit Oil, Pesea Gratissima (Avocado) Oil, Camellia Sinensis Leaf Extract, Water, Calendula Officinalis Flower Extract, Salicylic Acid, Sodium Hydroxide

PACKAGE LABEL

Perk Up

Lip & Cheek Treat

Broad Spectrum Sunscreen SPF 40

0.06 oz./ 4.5g